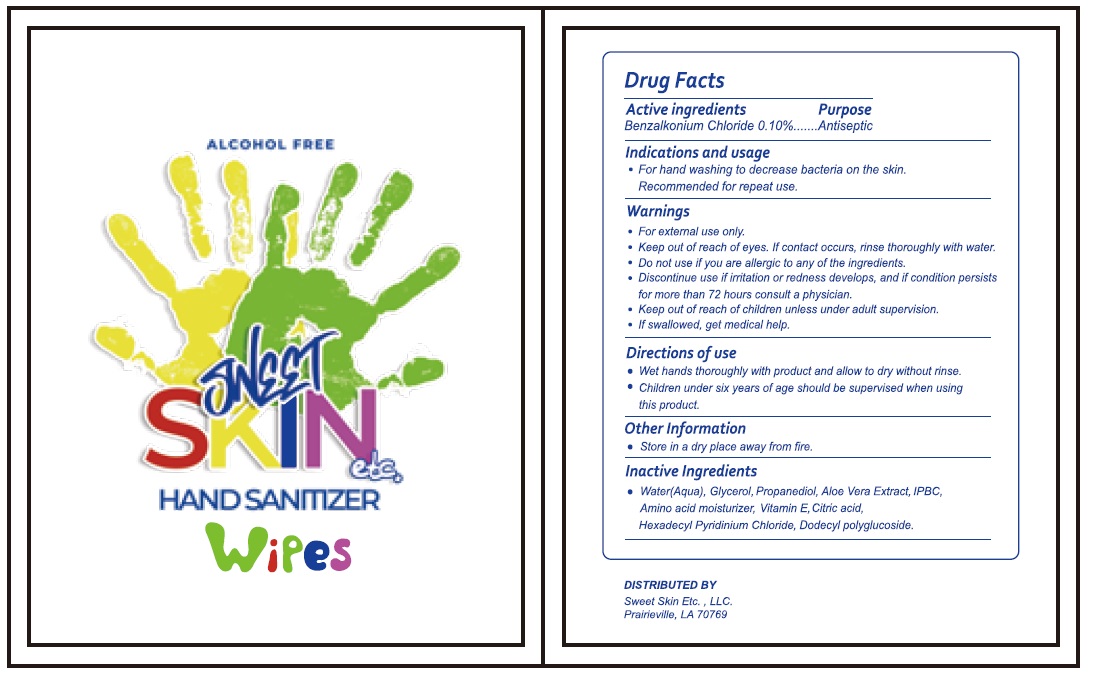 DRUG LABEL: Sweet Skin Etc Hand Sanitizer Wipes
NDC: 79891-002 | Form: CLOTH
Manufacturer: DOBOLV (QUANZHOU) PAPER CO., LTD
Category: otc | Type: HUMAN OTC DRUG LABEL
Date: 20201030

ACTIVE INGREDIENTS: BENZALKONIUM CHLORIDE 0.10 g/100 mL
INACTIVE INGREDIENTS: WATER; GLYCERIN; PROPANEDIOL; ALOE VERA LEAF; IODOPROPYNYL BUTYLCARBAMATE; BETAINE; .ALPHA.-TOCOPHEROL; CITRIC ACID MONOHYDRATE; CETYLPYRIDINIUM CHLORIDE ANHYDROUS; LAURYL GLUCOSIDE

SWEET SKIN etc. HAND SANITIZER Wipes

Active ingredients

Benzalkonium Chloride 0.10%

Purpose

Antiseptic

Indications and usage

• For hand washing to decrease bacteria on the skin.

Recommended for repeat use.

Warnings

• For external use only.

• Keep out of reach of eyes. If contact occurs, rinse thoroughly with water.

• Do not use if you are allergic to any one of the ingredients.

• Discontinue use if irritation or redness develops, and if condition persists for more than 72 hours consult a physician.

• Keep out of reach of children unless under adult supervision.

• If swallowed, get medical help.

Directions of use

• Wet hands thoroughly with product and allow to dry without rinse.

• Children under six years of age should be supervised when using this product.

Other Information

• Store in a dry place away from fire.

Inactive Ingredients

• Water (Aqua), Glycerol, Propanediol, Aloe Vera Extract, IPBC, Amino acid moisturizer, Vitamin E, Citric acid, Hexadecyl Pyridinium Chloride, Dodecyl polyglucoside.

ALCOHOL FREE

DISTRIBUTED BY

Sweet Skin Etc. , LLC.

Prairieville, LA 70769